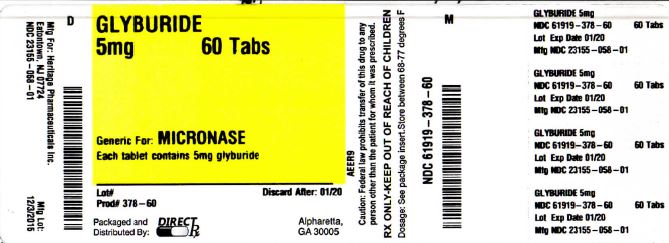 DRUG LABEL: GLYBURIDE
NDC: 61919-378 | Form: TABLET
Manufacturer: DirectRX
Category: prescription | Type: HUMAN PRESCRIPTION DRUG LABEL
Date: 20151204

ACTIVE INGREDIENTS: GLYBURIDE 5 mg/1 1
INACTIVE INGREDIENTS: LACTOSE MONOHYDRATE; CELLULOSE, MICROCRYSTALLINE; MAGNESIUM STEARATE; FD&C BLUE NO. 1

GLYBURIDE